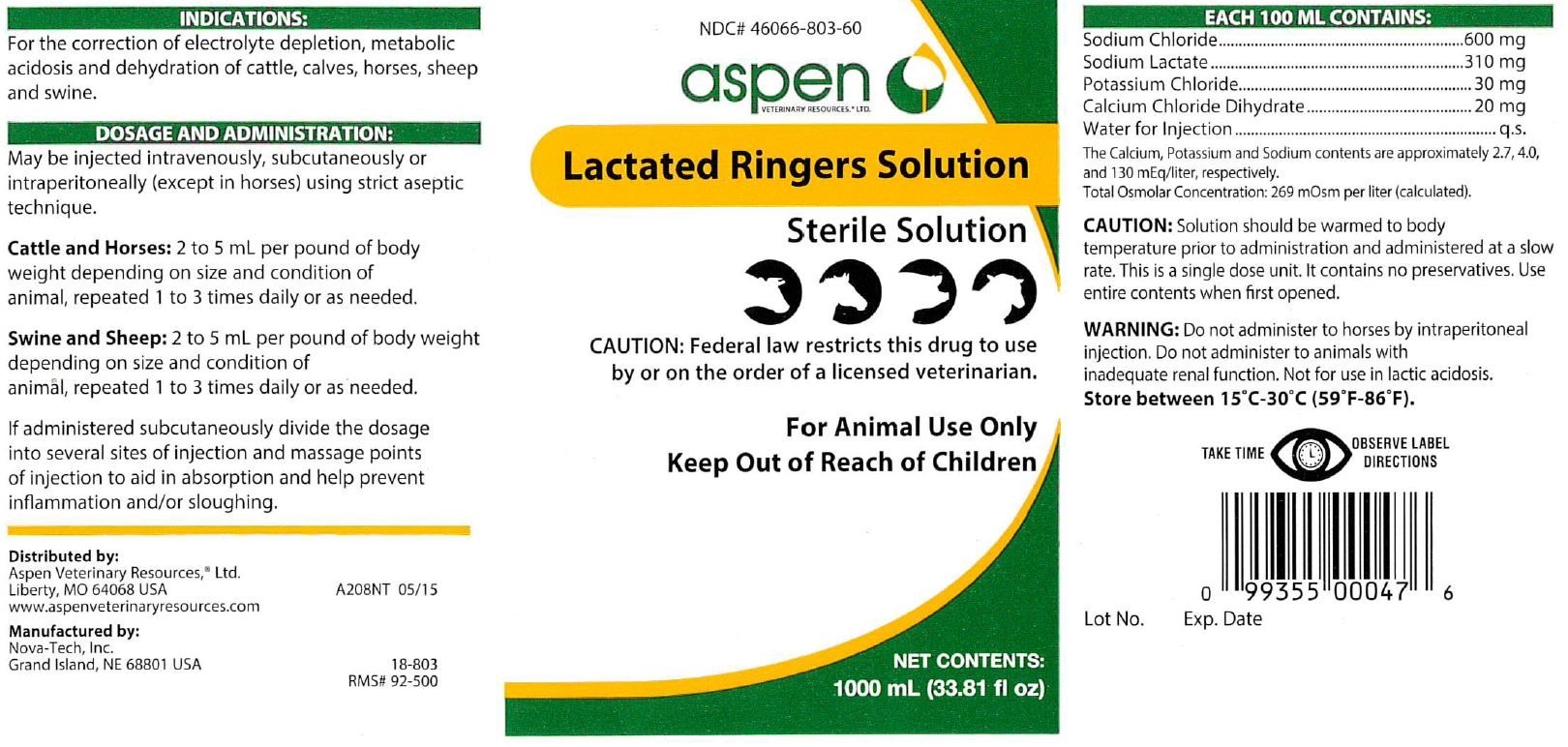 DRUG LABEL: Lactated Ringers Solution
NDC: 46066-803 | Form: INJECTION, SOLUTION
Manufacturer: Aspen Veterinary
Category: animal | Type: PRESCRIPTION ANIMAL DRUG LABEL
Date: 20240424

ACTIVE INGREDIENTS: Sodium Chloride 600 mg/100 mL; Sodium Lactate 310 mg/100 mL; Potassium Chloride 30 mg/100 mL; Calcium Chloride 20 mg/100 mL

Lactated Ringers Solution

INFORMATION FOR OWNERS/CAREGIVERS

Sterile Solution

CAUTION:

Federal law restricts this drug to use by or on the order of a licensed veterinarian.

VETERINARY INDICATIONS

FOR ANIMAL USE ONLY

KEEP OUT OF REACH OF CHILDREN

INFORMATION FOR OWNERS/CAREGIVERS

Net Contents: 1000 mL (33.81 fl oz)

INDICATIONS:

For the correction of electrolyte depletion, metabolic acidosis and dehydration of cattle, calves, horses, sheep and swine.

DOSAGE AND ADMINISTRATION:

May be injected intravenously, subcutaneously or intraperitoneally (except in horses) using strict aseptic technique.

Cattleand Horses: 2 to 5 mL per pound of body weight depending on size and condition of animal, repeated 1 to 3 times daily or as needed.

Swineand Sheep: 2 to 5 mL per pound of body weight depending on size and condition of animal, repeated 1 to 3 times daily or as needed.

If administered subcutaneously divide the dosage into several sites of injection and massage points of injection to aid in absorption and help prevent inflammation and/or sloughing.

WARNINGS AND PRECAUTIONS

TAKE TIME OBSERVE LABEL DIRECTIONS

DOSAGE FORMS AND STRENGTHS

EACH 100 ML CONTAINS:
Sodium Chloride...................................600 mg
Sodium Lactate....................................310 mg
Potassium Chloride.................................30 mg
Calcium Chloride Dihydrate......................20 mg
Water for Injection......................................q.s.
The Calcium, Potassium and Sodium contents are approximately 2.7, 4.0, and 130 mEq/liter, respectively.
Total Osmolar Concentration: 269 mOsm per liter (calculated).

CAUTION:

Solution should be warmed to body temperature prior to administration and administered at a slow rate. This is a single dose unit. It contains no preservatives. Use entire contents when first opened.

WARNING:

Do not administer to horses by intraperitoneal injection. Do not administer to animals with inadequate renal function. Not for use in lactic acidosis.

STORAGE AND HANDLING

Store between 15°C - 30°C (59°F - 86°F).

INFORMATION FOR OWNERS/CAREGIVERS

Distributed by:
Aspen Veterinary Resources, ® Ltd.
Liberty, MO 64068 USA

www.aspenveterinaryresources.com

A208NT

05/15

Manufactured by:
Nova-Tech, Inc.
Grand Island, NE 68801 USA

18-803

RMS# 92-500

NDC# 46066-803-60

Lot No.

Exp. Date